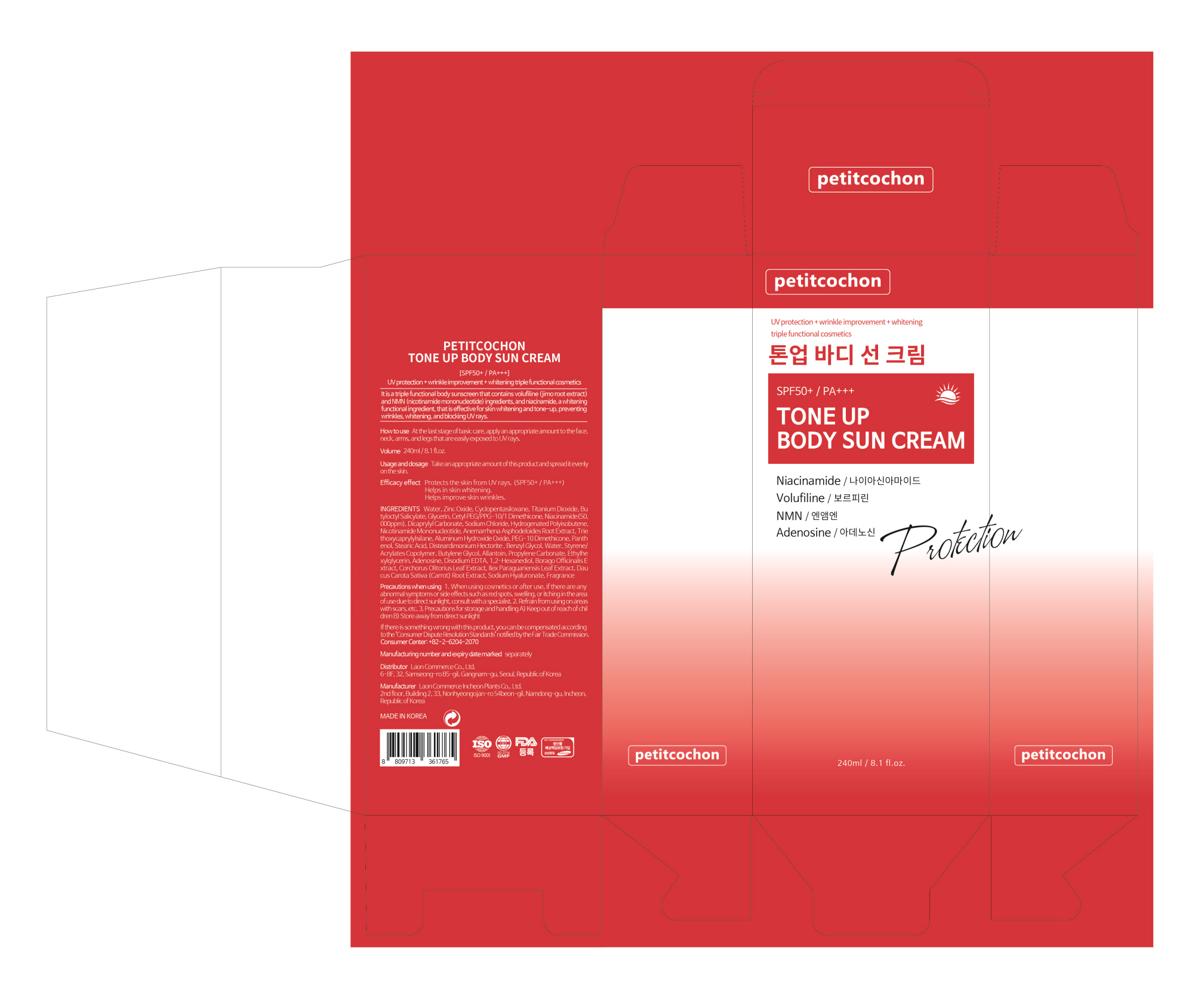 DRUG LABEL: PETITCOCHON TONE UP BODY SUN
NDC: 82083-0022 | Form: CREAM
Manufacturer: LAON COMMERCE co ltd
Category: otc | Type: HUMAN OTC DRUG LABEL
Date: 20230711

ACTIVE INGREDIENTS: ADENOSINE 0.04 g/100 mL; NIACINAMIDE 2 g/100 mL
INACTIVE INGREDIENTS: WATER

ACTIVE INGREDIENT

Niacinamide, Adenosine

INACTIVE INGREDIENT

Water
Zinc Oxide
Cyclopentasiloxane
Titanium Dioxide
Butyloctyl Salicylate
Glycerin
Cetyl PEG/PPG-10/1 Dimethicone
Dicaprylyl Carbonate
Sodium Chloride
Hydrogenated Polyisobutene
Nicotinamide Mononucleotide
Anemarrhena Asphodeloides Root Extract
Triethoxycaprylylsilane
Aluminum Hydroxide Oxide
PEG-10 Dimethicone
Panthenol
Stearic Acid
Disteardimonium Hectorite
Benzyl Glycol
Styrene/Acrylates Copolymer
Butylene Glycol
Allantoin
Propylene Carbonate
Ethylhexylglycerin
Disodium EDTA
1,2-Hexanediol
Borago Officinalis Extract
Corchorus Olitorius Leaf Extract
Ilex Paraguariensis Leaf Extract
Daucus Carota Sativa (Carrot) Root Extract
Sodium Hyaluronate
Fragrance

PURPOSE

skin protect

KEEP OUT OF REACH OF THE CHILDREN

INDICATIONS AND USAGE

How to use; At the last stage of basic care, apply an appropriate amount to the face, neck, arms, and legs that are easily exposed to UV rays.

WARNINGS

Precautions when using

1. When using cosmetics or after use, if there are any abnormal symptoms or side effects such as red spots, swelling, or itching in the area of use due to direct sunlight, consult with a specialist.

2. Refrain from using on areas with scars, etc.

3. Precautions for storage and handling

A) Keep out of reach of children

B) Store away from direct sunlight.

DOSAGE AND ADMINISTRATION

topical use only